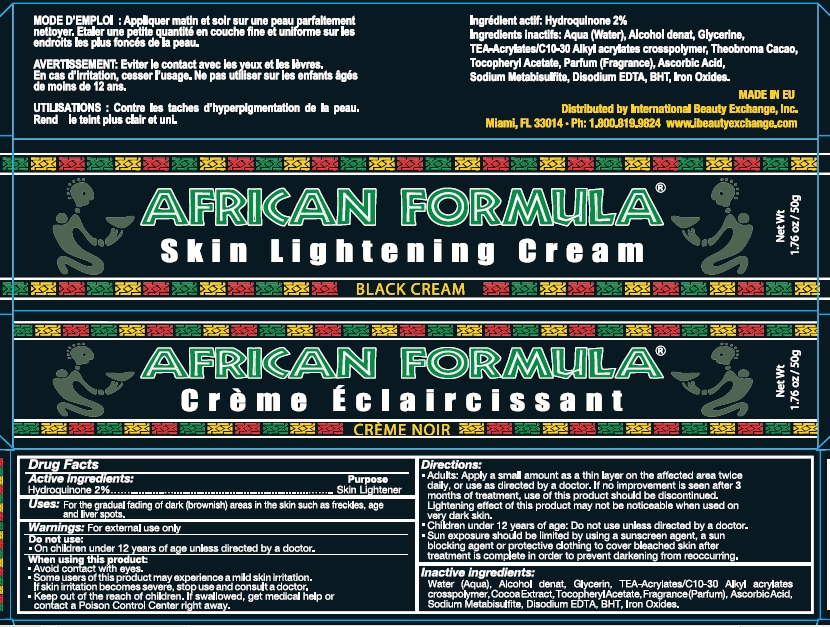 DRUG LABEL: African Formula Black
NDC: 66129-102 | Form: CREAM
Manufacturer: International Beauty Exchange
Category: otc | Type: HUMAN OTC DRUG LABEL
Date: 20110329

ACTIVE INGREDIENTS: HYDROQUINONE 1 g/50 g
INACTIVE INGREDIENTS: WATER; ALCOHOL; GLYCERIN; CARBOMER COPOLYMER TYPE A; COCOA BUTTER; .ALPHA.-TOCOPHEROL ACETATE, D-; ASCORBIC ACID; SODIUM METABISULFITE; EDETATE DISODIUM; BUTYLATED HYDROXYTOLUENE

Drug Facts

ACTIVE INGREDIENT

Hydroquinone 2%

WARNINGS

For external use only

PURPOSE

Skin Lightener

DO NOT USE

On children under 12 years of age unless directed by a doctor

WHEN USING

Avoid contact with eyes.

KEEP OUT OF REACH OF CHILDREN

If swallowed, get medical help or contact a Poison Control Center right away.